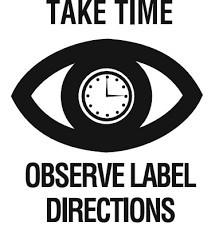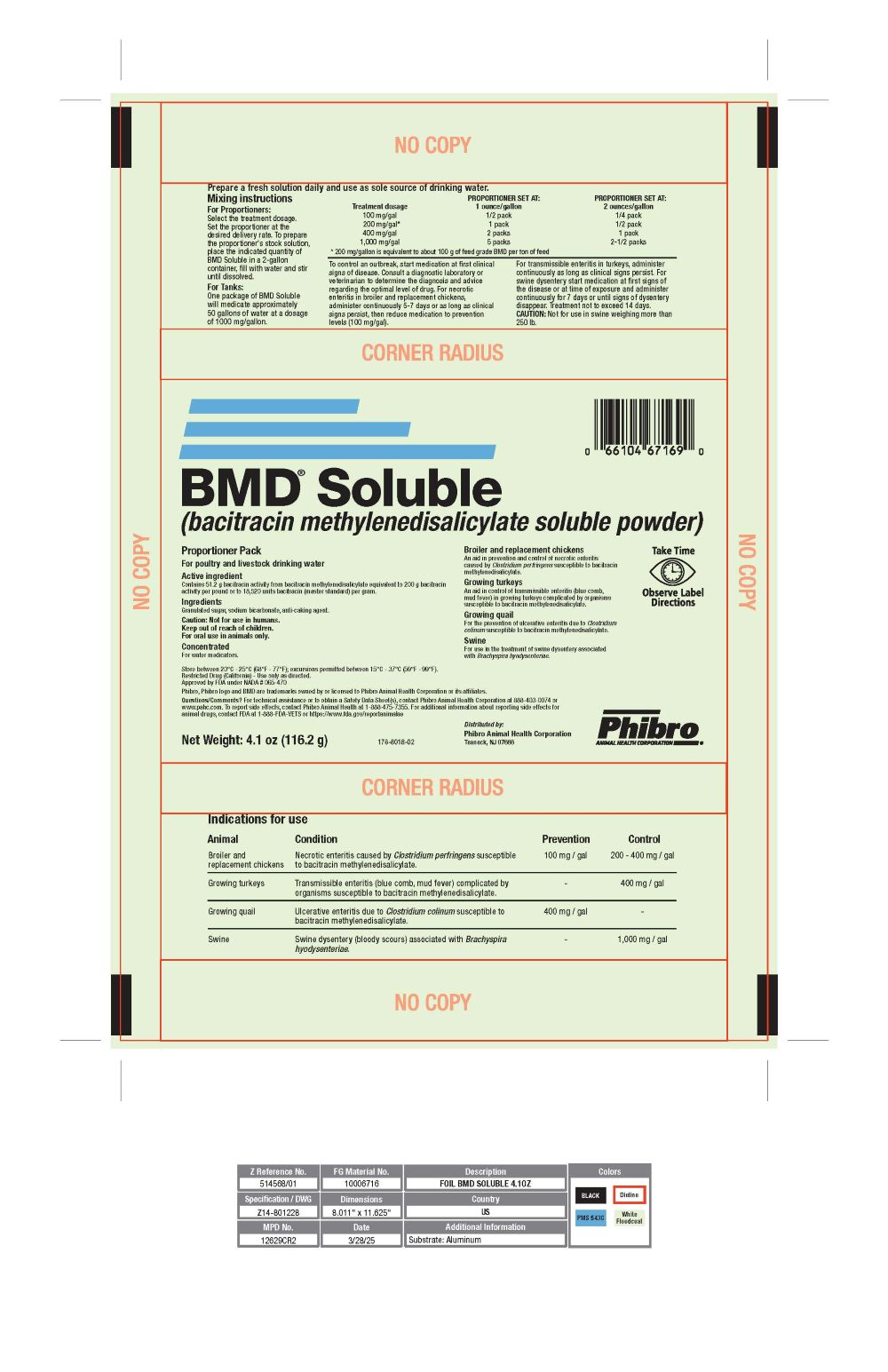 DRUG LABEL: BMD Soluble
NDC: 66104-1320 | Form: POWDER, FOR SOLUTION
Manufacturer: Phibro Animal Health
Category: animal | Type: OTC TYPE A MEDICATED ARTICLE ANIMAL DRUG LABEL
Date: 20260122

ACTIVE INGREDIENTS: BACITRACIN METHYLENEDISALICYLATE 200 mg/0.45 kg

BMD® Soluble

BMD® Soluble

(bacitracin methylenedisalicylate soluble powder)

Proportioner Pack

For poultry and livestock drinking water

INDICATIONS AND USAGE

Broiler and replacement chickens

An aid in prevention and control of necrotic enteritis caused by Clostridium perfringens susceptible to bacitracin methylenedisalicylate.

Growing turkeys

An aid in control of transmissible enteritis (blue comb, mud fever) in growing turkeys complicated by organisms susceptible to bacitracin methylenedisalicylate.

Growing quail

For the prevention of ulcerative enteritis due to Clostridium colinum susceptible to bacitracin methylenedisalicylate.

Swine

For use in the treatment of swine dysentery associated with Brachyspira hyodysenteriae.

DESCRIPTION

Active ingredient

Contains 51.2 g bacitracin activity from bacitracin methylenedisalicylate equivalent to 200 g bacitracin activity per pound or to 18,520 units bacitracin (master standard) per gram.

Ingredients

Granulated sugar, sodium bicarbonate, anti-caking agent.

Caution

Not for use in humans. Keep out of reach of children.
For oral use in animals only.

Not for use in humans.
Keep out of reach of children.
For oral use in animals only.

Concentrated

For water medicators.

Directions for use

Animal | Condition | Prevention | Control
Broiler and replacement chickens | Necrotic enteritis caused by Clostridium perfringens susceptible to bacitracin methylenedisalicylate. | 100 mg / gal | 200 - 400 mg / gal
Growing turkeys | Transmissible enteritis (blue comb, mud fever) complicated by organisms susceptible to bacitracin methylenedisalicylate. | - | 400 mg / gal
Growing quail | Ulcerative enteritis due to Clostridium colinum susceptible to bacitracin methylenedisalicylate.. | 400 mg / gal | -
Swine | Swine dysentery (bloody scours) associated with Brachyspira hyodysenteriae. | - | 1,000 mg / gal

STORAGE AND HANDLING

Store between 20°C -25°C (68°F - 77°F); excursions permitted between 15°C - 37°C (59°F - 99°F).

Restricted Drug (California) - Use only as directed.

Approved by FDA under NADA # 065-470

Phibro, Phibro logo and BMD are trademarks owned by or licensed to Phibro Animal Health Corporation or its affiliates.

Questions/Comments? For technical assistance or to obtain a Safety Data Sheet(s), contact Phibro Animal Health Corporation at 888-403-0074 or
www.pahc.com. To report side effects, contact Phibro Animal Health at 1-888-475-7355. For additional information about reporting side effects for
animal drugs, contact FDA at 1-888-FDA-VETS or https://www.fda.gov/reportanimalae

DOSAGE AND ADMINISTRATION

Prepare a fresh solution daily and use as sole source of drinking water.

Mixing instructions

For Proportioners

Select the treatment dosage. Set the proportioner at the desired delivery rate. To prepare the proportioner's stock solution, place the indicated quantity of BMD Soluble in a 2-gallon container, fill with water and stir until dissolved.

For Tanks

One package of BMD Soluble will medicate approximately 50 gallons of water at a dosage of 1000 mg/gallon.

Treatment dosage | PROPORTIONER SET AT: 1 ounce/gallon | PROPORTIONER SET AT: 2 ounces/gallon
100 mg/gal | 1/2 pack | 1/4 pack
200 mg/gal [200 mg/gallon is equivalent to about 100 g of feed grade BMD per ton of feed] | 1 pack | 1/2 pack
400 mg/gal | 2 packs | 1 pack
1,000 mg/gal | 5 packs | 2-1/2 packs

*200 mg/gallon is equivalent to about 100 g of feed grade BMD per ton of feed

To control an outbreak, start medication at first clinical signs of disease. Consult a diagnostic laboratory or veterinarian to determine the diagnosis and advice regarding the optimal level of drug. For necrotic enteritis in broiler and replacement chickens, administer continuously 5-7 days or as long as clinical signs persist, then reduce medication to prevention levels (100 mg/gal).

For transmissible enteritis in turkeys, administer continuously as long as clinical signs persist. For swine dysentery start medication at first signs of the disease or at time of exposure and administer continuously for 7 days or until signs of dysentery disappear. Treatment not to exceed 14 days.

CAUTION: Not for use in swine weighing more than 250 lb.

Distributed by:

Phibro Animal Health Corporation

Teaneck, NJ 07666

Take Time Statement

Net Weight 4.1 oz (116.2 g)

176-8018-01

PRINCIPAL DISPLAY PANEL - bag label

BMD Soluble Label